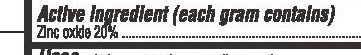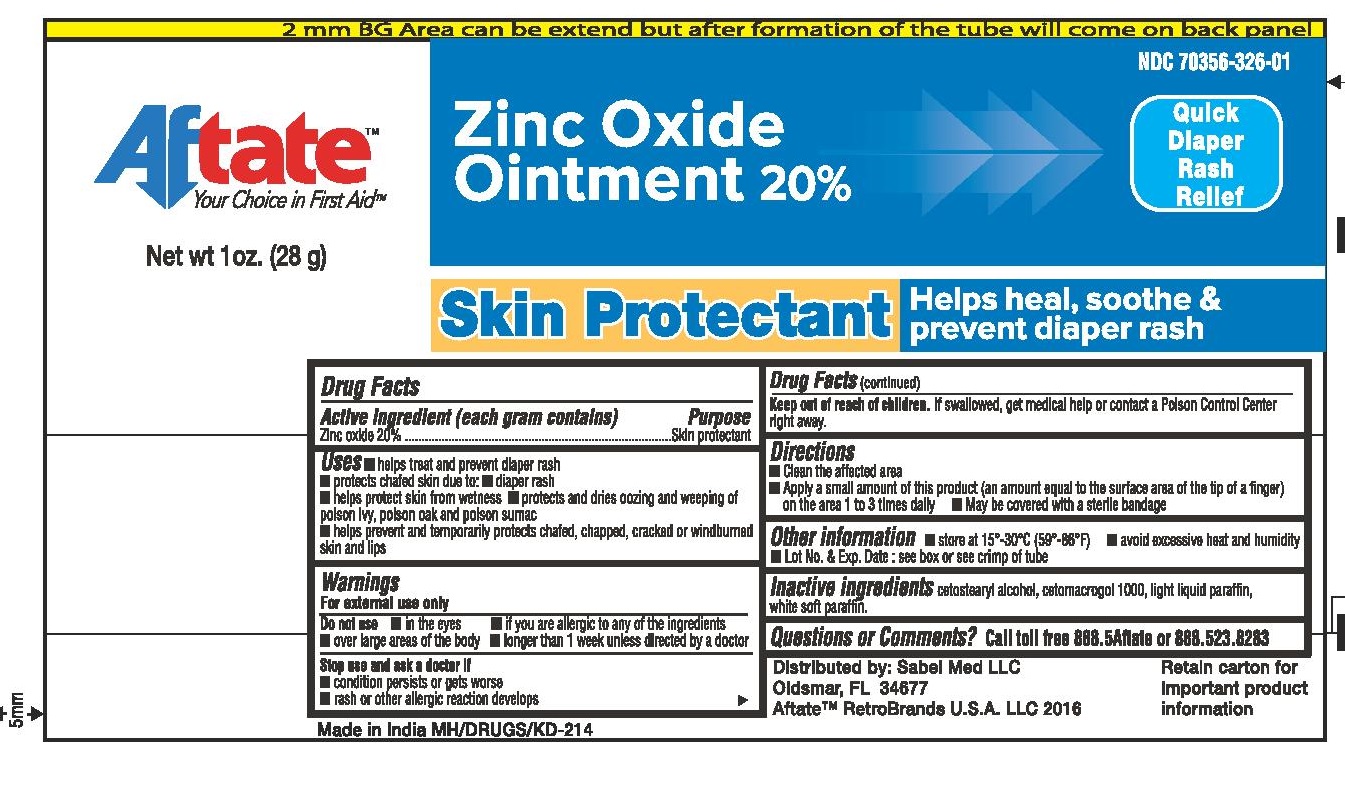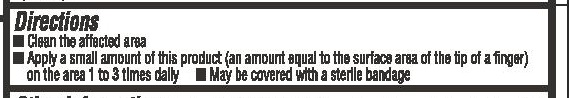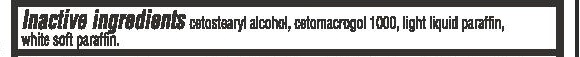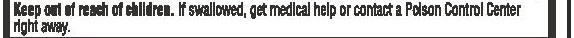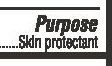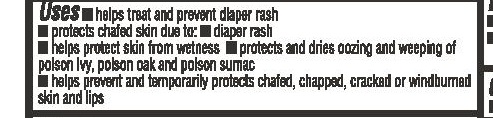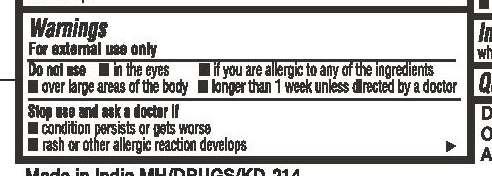 DRUG LABEL: Aftate Zinc Oxide
NDC: 70356-326 | Form: OINTMENT
Manufacturer: Sabel Med LLC
Category: otc | Type: HUMAN OTC DRUG LABEL
Date: 20160406

ACTIVE INGREDIENTS: ZINC OXIDE 0.2 g/1 g
INACTIVE INGREDIENTS: PARAFFIN; MINERAL OIL; CETOSTEARYL ALCOHOL; CETETH-20

Zinc Oxide Ointment (1 oz and 2 oz)